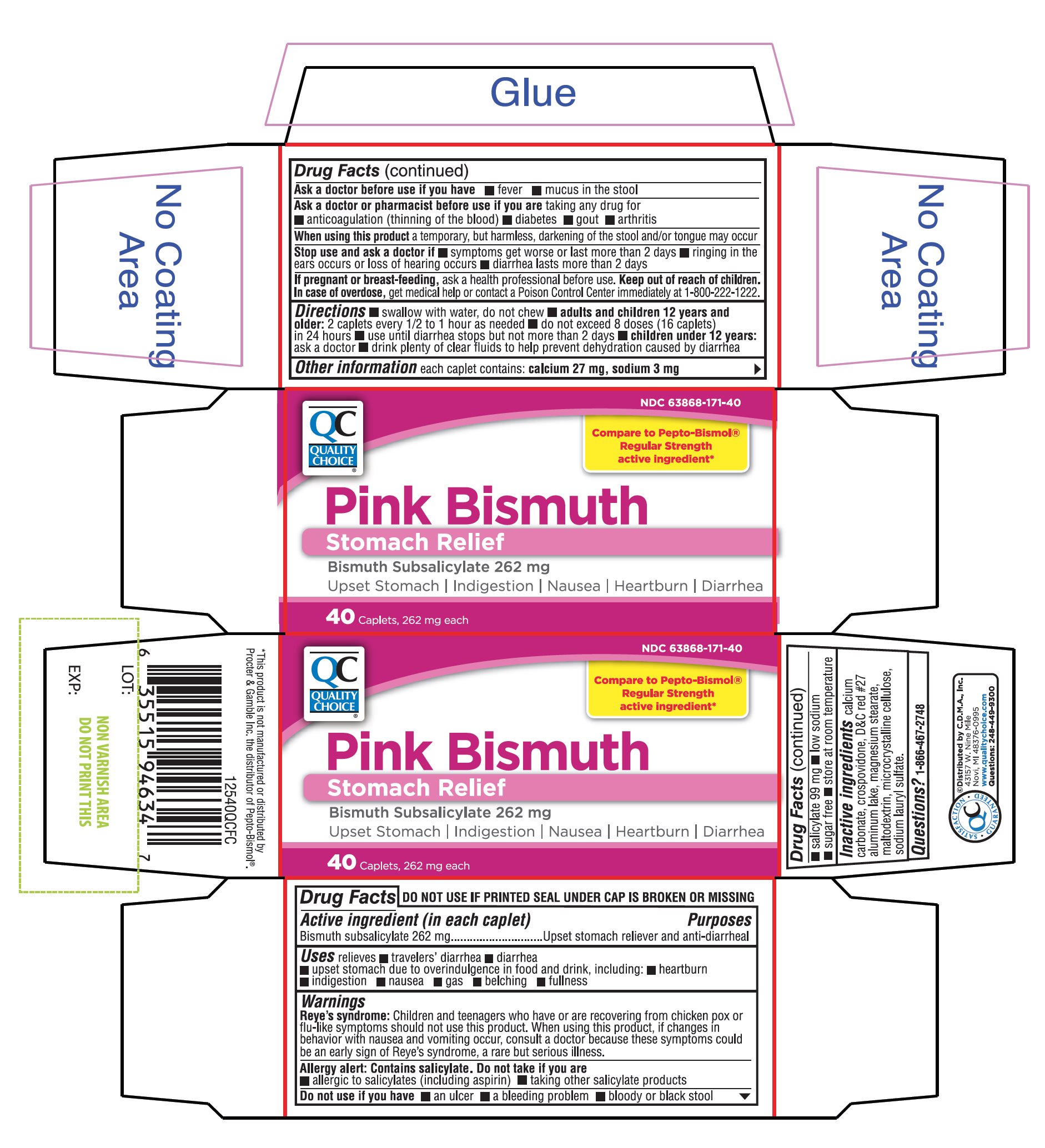 DRUG LABEL: QC Pink Bismuth
NDC: 63868-171 | Form: TABLET, FILM COATED
Manufacturer: QUALITY CHOICE (CHAIN DRUG MARKETING ASSOCIATION)
Category: otc | Type: HUMAN OTC DRUG LABEL
Date: 20251203

ACTIVE INGREDIENTS: BISMUTH SUBSALICYLATE 262 mg/1 1
INACTIVE INGREDIENTS: CALCIUM CARBONATE; CROSPOVIDONE (120 .MU.M); D&C RED NO. 27; MAGNESIUM STEARATE; MALTODEXTRIN; MICROCRYSTALLINE CELLULOSE; SODIUM LAURYL SULFATE

Quality Choice Pink Bismuth Subsalicylate 262 mg

Drug Facts

Active ingredient (in each caplet)

Bismuth subsalicylate 262 mg

Purpose

Upset stomach reliever and anti-diarrheal

Uses

relieves:

■ travelers’ diarrhea

■ diarrhea

■ upset stomach due to overindulgence in food and drink, including: ■ heartburn ■ indigestion ■ nausea ■ gas ■ belching ■ fullness

WARNINGS

Reye's syndrome:Children and teenagers who have or are recovering from chicken pox or flu-like symptoms should not use this product. When using this product, if changes in behavior with nausea and vomiting occur, consult a doctor because these symptoms could be an early sign of Reye's syndrome, a rare but serious illness.

Allergy alert: Contains salicylate. Do not take if you are

- allergic to salicylates (including aspirin)
- taking other salicylate products.

Do not use if you have

- an ulcer
- a bleeding problem
- bloody or black stool

Ask a doctor before use if you have

- fever
- mucus in the stool

Ask a doctor or pharmacist before use if you are

taking any drug for

- anticoagulation (thinning the blood)
- diabetes
- gout
- arthritis

When using this product

a temporary but harmless darkening of the stool and/or tongue may occur.

Stop use and ask a doctor if

- symptoms get worse or last more than 2 days
- ringing in the ears or loss of hearing occurs
- diarrhea lasts more than 2 days

PREGNANCY OR BREAST FEEDING

If pregnant or breast-feeding,ask a health professional before use.

Keep out of reach of children.

OVERDOSAGE

In case of overdose, get medical help or contact a Poison Control Center immediately at 1-800-222-1222

Directions

- swallow with water, do not chew
- adults and children 12 years and older:2 caplets every 1/2 to 1 hour as needed
- do not exceed 8 doses (16 caplets) in 24 hours
- use until diarrhea stops but not more than 2 days
- children under 12 years:ask a doctor
- drink plenty of clear fluids to help prevent dehydration caused by diarrhea

Other Information

- each caplet contains: calcium 27 mg, sodium 3 mg
- salicylate 99 mg
- low sodium
- sugar free
- store at room temperature.

Questions or comments?

1-866-467-2748

Inactive Ingredients

calcium carbonate, crospovidone, D&C red #27 aluminum lake, magnesium stearate, maltodextrin, microcrystalline cellulose, sodium lauryl sulfate.

PACKAGE LABEL

NDC# 63868-171-40

Compare to Pepto-Bismol® Regular Strength the active ingredient*

Pink Bismuth

Stomach Relief

Bismuth Subsalicylate 262mg

Upset stomach Indigestion, Nausea, Heartburn, Diarrhea

Package Contains One Bottle

40 Caplets

QC SATISFACTION GUARANTEED

Distributed by C.D.M.A., Inc.

43157 W. Nine Mile

Novi MI 48376-0995

www.qualitychoice.com

Questions: 248-449-9300

* This product is not manufactured or distributed by Procter & Gamble Inc., the distributor of Pepto-Bismol®.